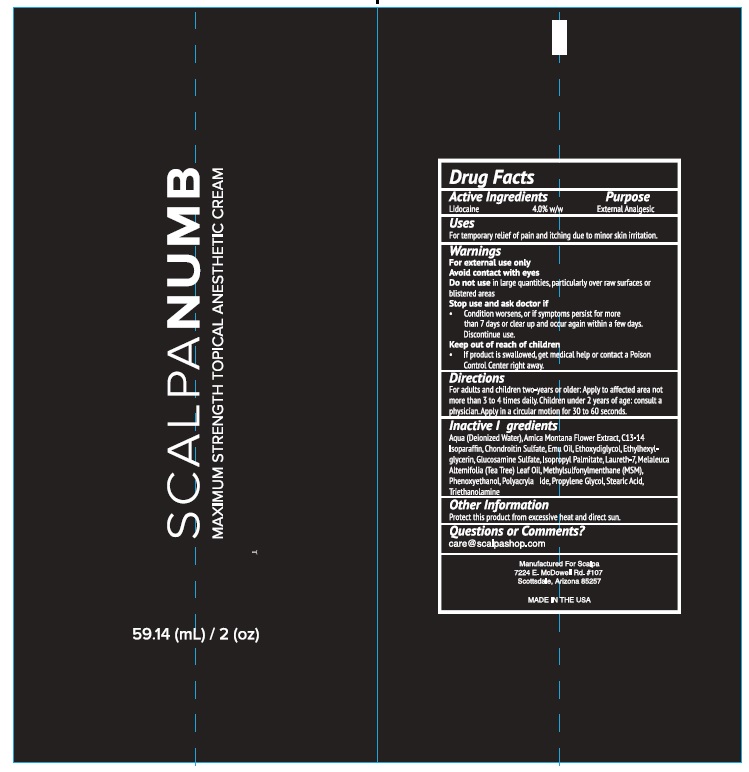 DRUG LABEL: Scalpanumb
NDC: 54723-001 | Form: CREAM
Manufacturer: Sambria Pharmaceuticals, LLC
Category: otc | Type: HUMAN OTC DRUG LABEL
Date: 20210917

ACTIVE INGREDIENTS: LIDOCAINE 4 g/100 mL
INACTIVE INGREDIENTS: WATER; ARNICA MONTANA FLOWER; C13-14 ISOPARAFFIN; SODIUM CHONDROITIN SULFATE (PORCINE; 5500 MW); EMU OIL; DIETHYLENE GLYCOL MONOETHYL ETHER; ETHYLHEXYLGLYCERIN; GLUCOSAMINE SULFATE; ISOPROPYL PALMITATE; LAURETH-7; MELALEUCA ALTERNIFOLIA LEAF; DIMETHYL SULFONE; PHENOXYETHANOL; POLYACRYLAMIDE (10000 MW); PROPYLENE GLYCOL; STEARIC ACID; TROLAMINE

Active ingredient

Lidocaine 4% w/w

Purpose

External Analgesic

Uses

For temporary relief of pain and itching due to minor skin irritations.

warnings

For external use only.
Avoid contact with eyes.

Do not use in large quantities, particularly over the raw surfaces or blistered area

Stop use and ask a doctor if

condition worsens, or if symptoms persists for more than 7 days or clear up and occur again within the few days. Discontinue use.

Directions

For adults and children two-years or older: Apply to affected area not more than 3 or 4 times daily. Children under 2 years of age: consult a physician.

Keep out of reach of children

If product is swallowed, get medical help or contact a Poison Control Center right away

Inactive ingredients

Aqua (Deionized Water), Arnica Montana Floweri Extract, C13-14 Isoparaffin, Chondroitin Sulfate, Emu Oil, Ethoxydiglycol, Ethylhexylglycerin, Glucosamine Sulfate, Isopropyl Palmitate, Laureth-7, Melaleuca Alternifolia (Tea Tree) Oil, Methylsulfonylmenthane (MSM), Phenoxyethanol, Polyacrylamide, Propylene Glycol, Stearic Acid, Triethanolamine.

Other information

Protect this product from excessive heat and direct sun.

Questions or comments?

care@scalpashop.com